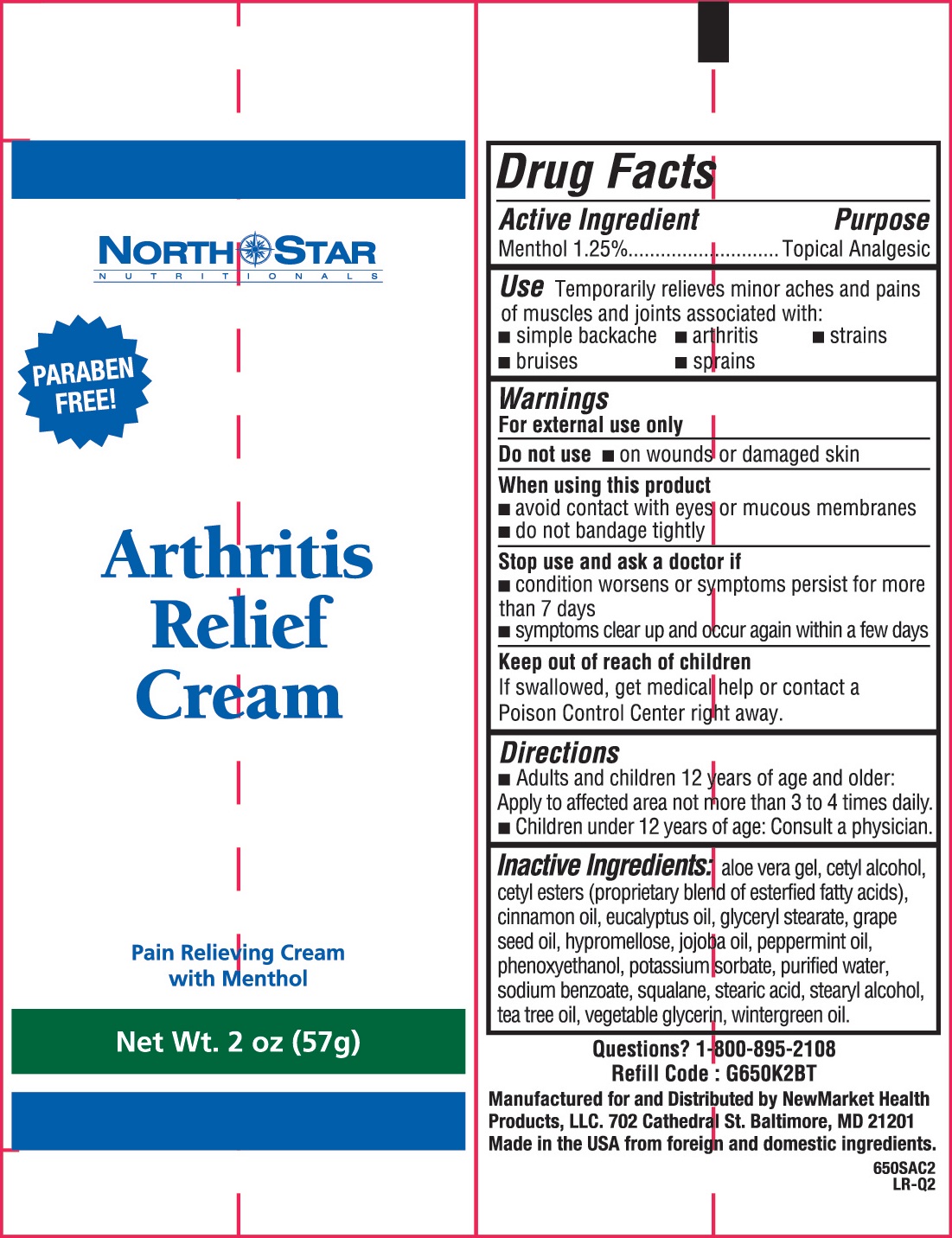 DRUG LABEL: Arthritis Relief
NDC: 50972-300 | Form: CREAM
Manufacturer: NewMarket Health Products LLC
Category: otc | Type: HUMAN OTC DRUG LABEL
Date: 20170501

ACTIVE INGREDIENTS: MENTHOL 12.5 mg/1 g
INACTIVE INGREDIENTS: ALOE VERA LEAF; CETYL ALCOHOL; CETYL ESTERS WAX; CINNAMON OIL; EUCALYPTUS OIL; GLYCERYL MONOSTEARATE; GRAPE SEED OIL; HYPROMELLOSES; JOJOBA OIL; PEPPERMINT OIL; PHENOXYETHANOL; POTASSIUM SORBATE; WATER; SODIUM BENZOATE; SQUALANE; STEARIC ACID; STEARYL ALCOHOL; TEA TREE OIL; METHYL SALICYLATE

Arthritis Relief Cream

Active Ingredient

Menthol 1.25%

Purpose

Topical Analgesic

Use

Temporarily relieves minor aches and pains of muscles and joints associated with:

- simple backache

- arthritis

- strains

- bruises

- sprains

Warnings

For external use only

Do not use

- on wounds or damaged skin

When using this product

- avoid contact with eyes or mucous membranes
- do not bandage tightly

Stop use and ask a doctor if

- condition worsens or symptoms persist for more than 7 days
- symptoms clear up and occur again within a few days

Keep out of reach of children.

If swallowed, get medical help or contact a Poison Control Center right away.

Directions

- Adult and children 12 years of age or older: Apply to affected area not more than 3 to 4 times daily.
- Children under 12 years of age: Consult a physician.

Inactive Ingredients:

aloe vera gel, cetyl alcohol, cetyl esters (proprietary blend of esterfied fatty acids), cinnamon oil, eucalyptus oil, glyceryl stearate, grape seed oil, hypromellose, jojoba oil, peppermint oil, phenoxyethanol, potassium sorbate, purified water, sodium benzoate, squalane, stearic acid, stearyl alcohol, tea tree oil, vegetable glycerin, wintergreen oil.

Questions?

1-800-895-2108